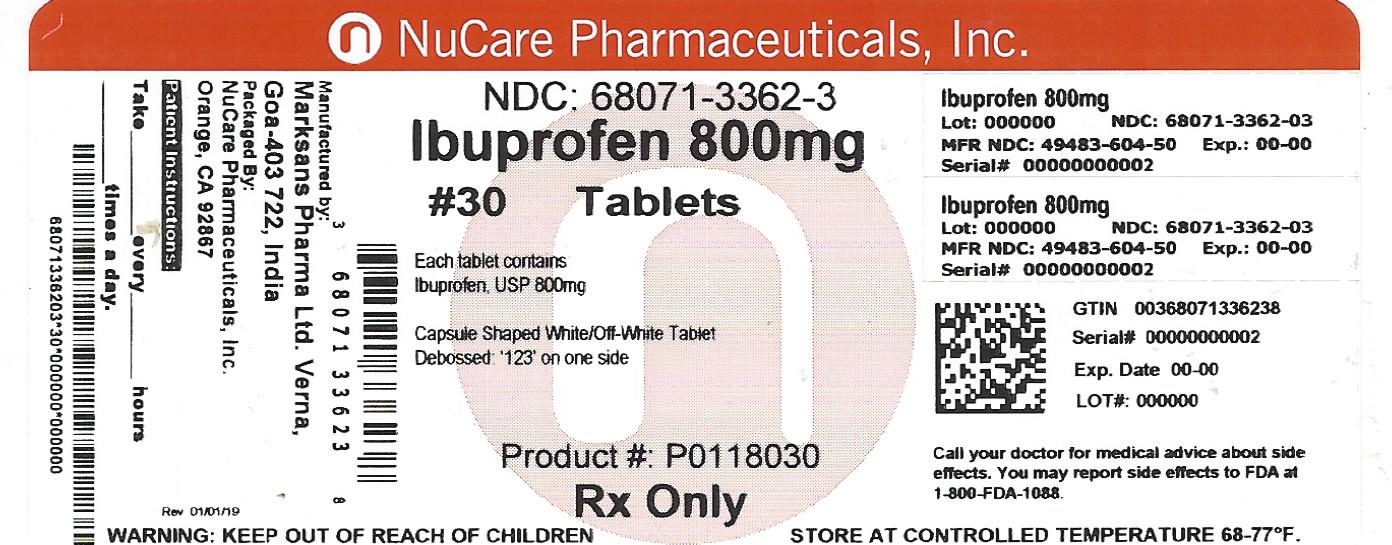 DRUG LABEL: IBUPROFEN
NDC: 68071-3362 | Form: TABLET, FILM COATED
Manufacturer: NuCare Pharmaceuticals,Inc.
Category: prescription | Type: HUMAN PRESCRIPTION DRUG LABEL
Date: 20240710

ACTIVE INGREDIENTS: IBUPROFEN 800 mg/1 1
INACTIVE INGREDIENTS: SILICON DIOXIDE; CROSCARMELLOSE SODIUM; MAGNESIUM STEARATE; CELLULOSE, MICROCRYSTALLINE; POLYETHYLENE GLYCOL, UNSPECIFIED; POLYVINYL ALCOHOL; STARCH, PREGELATINIZED CORN; TALC; TITANIUM DIOXIDE

HOW SUPPLIED

NDC 68071-3362-0 Bottles of 12

NDC 68071-3362-5 Bottles of 15

NDC 68071-3362-2 Bottles of 20

NDC 68071-3362-1 Bottles of 21

NDC 68071-3362-3 Bottles of 30

NDC 68071-3362-4 Bottles of 40

NDC 68071-3362-6 Bottles of 60

NDC 68071-3362-9 Bottles of 90